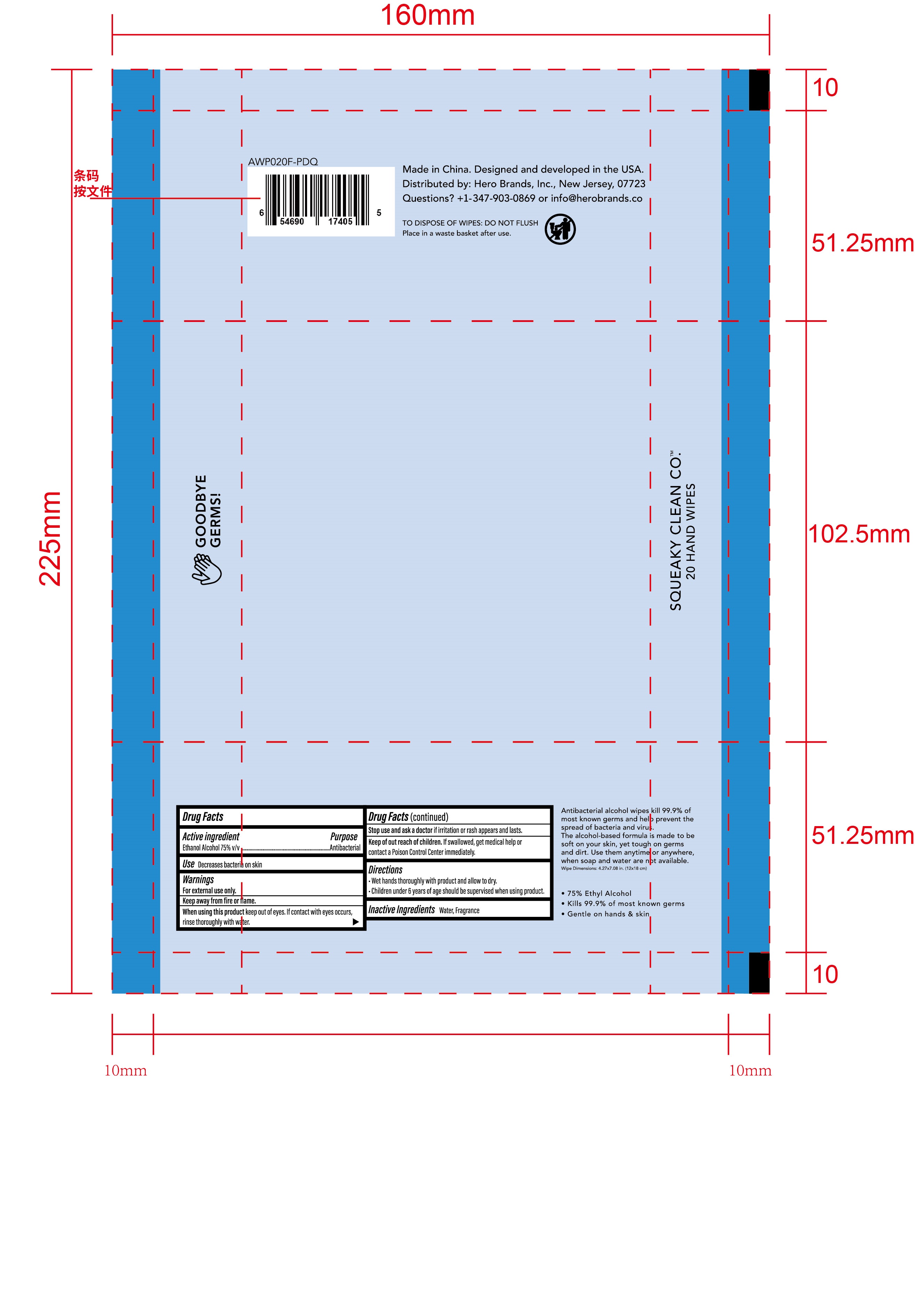 DRUG LABEL: 20 Pack Alcohol Hand Wipes - Fresh
NDC: 90114-201 | Form: CLOTH
Manufacturer: Hero Brands, Inc.
Category: otc | Type: HUMAN OTC DRUG LABEL
Date: 20200828

ACTIVE INGREDIENTS: ALCOHOL 75 mL/100 1
INACTIVE INGREDIENTS: LAVENDER OIL; WATER

90114-201 20 Pack Alcohol Hand Wipes - Aloe zhuji jianhe

Active Ingredient(s)

Ethanol Alcohol 75% v/v, Antibacterial

Purpose

Antibacterial, Hand wipes

Use

Decreases bacteria on skin.

Warnings

For external use only. Keep away from fire or flame

Do not use

- in children less than 2 months of age
- on open skin wounds

When using this product keep out of eyes, If contact with eyes occurs, rinse thoroughly with water.

Stop use and ask a doctor if irritation or rash appears and lasts.

Keep out of reach of children. If swallowed, get medical help or contact a Poison Control Center immediately.

Directions

- Wet hands thoroughly with product and allow to dry.
- Children under 6 years of age should be supervised when using product.

Inactive ingredients

Water, Fragrance.

Package Label - Principal Display Panel

20 HAND WIPES NDC: 90114-201-01